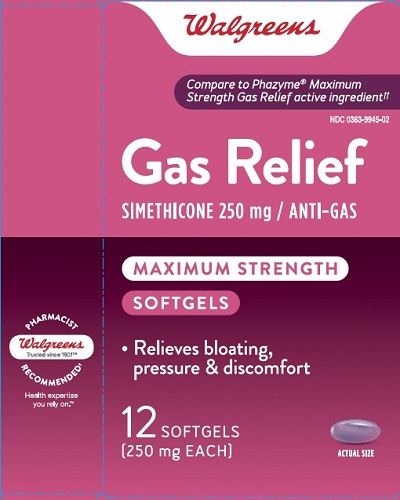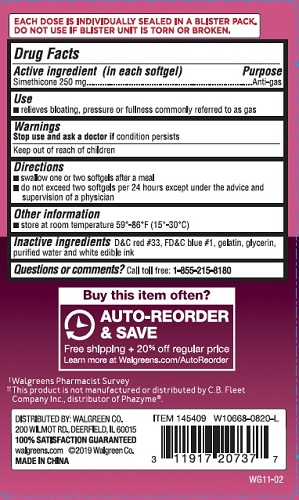 DRUG LABEL: Simethicone
NDC: 0363-9945 | Form: CAPSULE, LIQUID FILLED
Manufacturer: WALGREEN CO.
Category: otc | Type: HUMAN OTC DRUG LABEL
Date: 20241121

ACTIVE INGREDIENTS: DIMETHICONE 250 mg/1 1
INACTIVE INGREDIENTS: D&C RED NO. 33; FD&C BLUE NO. 1; GELATIN, UNSPECIFIED; GLYCERIN; WATER

MAXIMUM STRENGTH GAS RELIEF

Active ingredient

Simethicone 250 mg

Purpose

Anti-gas

Uses

relieves bloating, pressure or fullness commonly referred to as gas

Warnings

Stop use and ask a doctor if

condition persists

Directions

- swallow one or two softgels after a meal
- do not exceed two softgels per 24 hours except under the advice and supervision of a physician

Other Information

- store at room temperature 59°-86°F (15°-30°C)

Inactive Ingredients

D&C red # 33, FD&C blue # 1, gelatin, glycerin, purified water and white edible ink

Questions or comments?

Call toll free: 1-855-215-8180